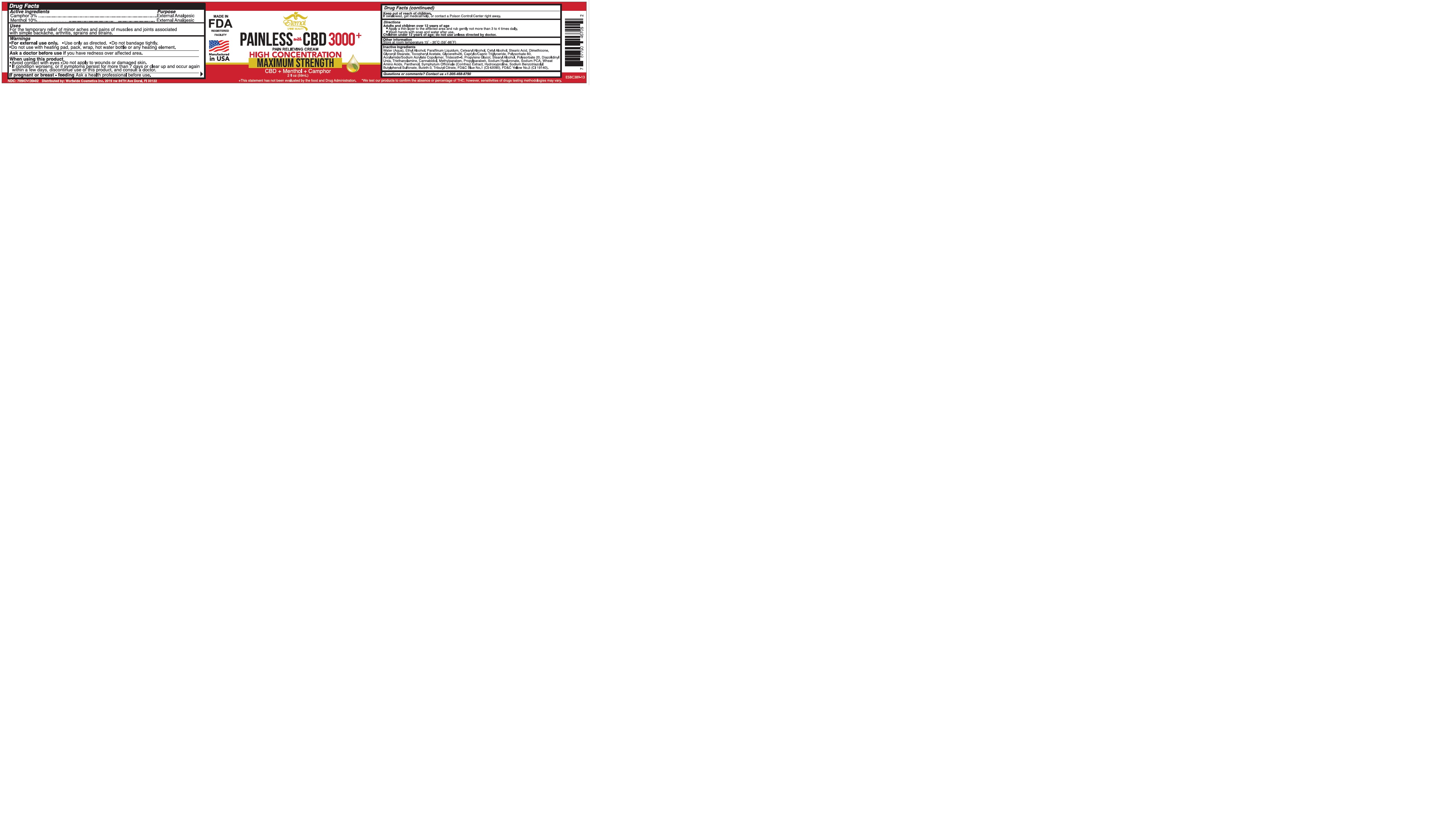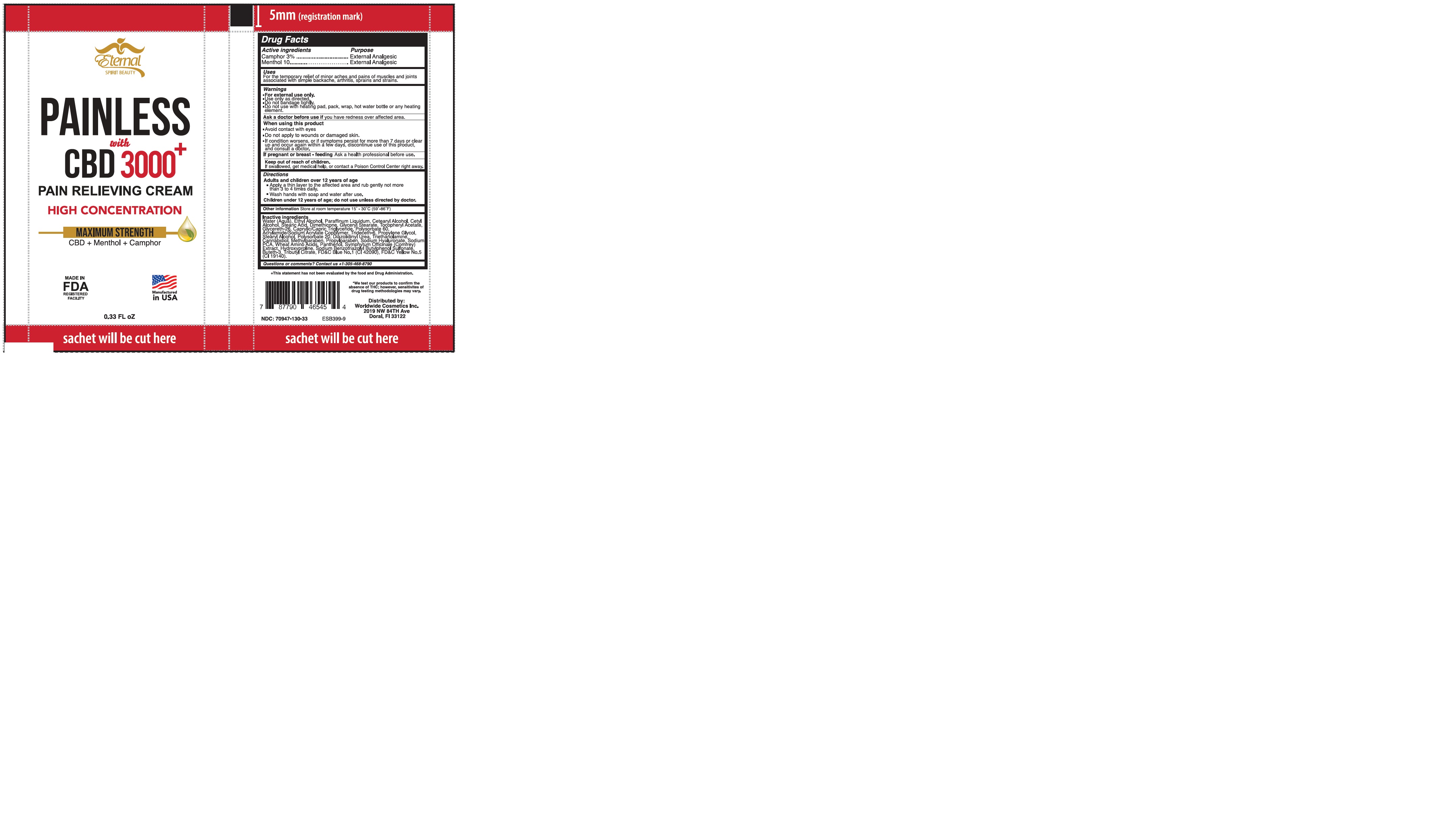 DRUG LABEL: ETERNAL SPIRIT BEAUTY PAINLESS WITH CBD 3000
NDC: 70947-130 | Form: CREAM
Manufacturer: Worldwide Cosmetics, Inc
Category: otc | Type: HUMAN OTC DRUG LABEL
Date: 20251117

ACTIVE INGREDIENTS: MENTHOL, UNSPECIFIED FORM 10 g/100 g; CAMPHOR (SYNTHETIC) 3 g/100 g
INACTIVE INGREDIENTS: SODIUM COCOYL WHEAT AMINO ACIDS; WATER; CETYL ALCOHOL; GLYCERETH-26; METHYLPARABEN; TRIBUTYL CITRATE; BUTETH-3; PANTHENOL; DIAZOLIDINYL UREA; CANNABIDIOL; HYALURONATE SODIUM; DIMETHICONE 1000; GLYCERIN; HYDROXYPROLINE; SYMPHYTUM OFFICINALE WHOLE; TRIDECETH-6; SODIUM BENZOTRIAZOLYL BUTYLPHENOL SULFONATE; CETOSTEARYL ALCOHOL; GLYCERYL STEARATE SE; ALCOHOL 95%; ACRYLAMIDE; MINERAL OIL; .ALPHA.-TOCOPHEROL ACETATE, D-; CAPRYLIC/CAPRIC/LAURIC TRIGLYCERIDE; POLYSORBATE 20; PROPYLPARABEN; STEARIC ACID

70947-130-02
70947-130-33

ACTIVE INGREDIENT

Camphor 3%

Menthol 10%

PURPOSE

External Analgesic

USES:

For the temporary relief of minor aches and pains of muscles and joints associated
with simple backache, arthritis, sprains and strains.

WARNINGS

For external use only.

Use only as directed.

Do not bandage tightly.

Do not use with heating pad, pack, wrap, hot water bottle or any heating element.

ASK A DOCTOR BEFORE USE IF YOU HAVE

Redness over affected area

WHEN USING

Avoid contact with eyes

Do not apply to wounds or damaged skin.

If confition worsens, or if symptoms persist for more than 7 days or clear up and occur again within a few days, discontinue use of this product, and consult a doctor.

PREGNANCY OR BREAST FEEDING

If pregnant or breast-feeding ask a proffesional before use

Keep out of reach of children. If swallowed, get medical help or call a Poison Control Center right away

DIRECTIONS:

Adults and children over 12 years of age

*Apply a thin layer to affected area and rub gently not more than 3 to 4 times a day.
*Wash hands with soap and water after use.
Children under 12 years of age; do not use unless directed by doctor

OTHER INFORMATION:

Store at room temperature 15° - 30°C (59° - 86°F)

INACTIVE INGREDIENT

Water (Aqua), Ethyl Alcohol, Paraffinum Liquidum, Cetearyl Alcohol, Cetyl Alcohol, Stearic Acid, Dimethicone, Glyceryl Stearate, Tocopheryl Acetate, Glycereth-26, Caprylic/Capric Triglyceride, Polysorbate 60, Acrylamide/Sodium Acrylate Copolymer, Trideceth-6, Propylene Glycol, Stearyl Alcohol, Polysorbate 20, Diazolidinyl Urea, Triethanolamine, Cannabidiol, Methylparaben, Propylparaben, Sodium Hyaluronate, Sodium PCA, Wheat Amino Acids, Panthenol, Symphytum Officinale (Comfrey) Extract, Hydroxyproline, Sodium Benzotriazolyl Butylphenol Sulfonate, Buteth-3, Tributyl Citrate, FD&C Blue No.1 (CI 42090), FD&C Yellow No.5 (CI 19140).

QUESTIONS OR COMMENTS?

Contact us +1-305-468-8790